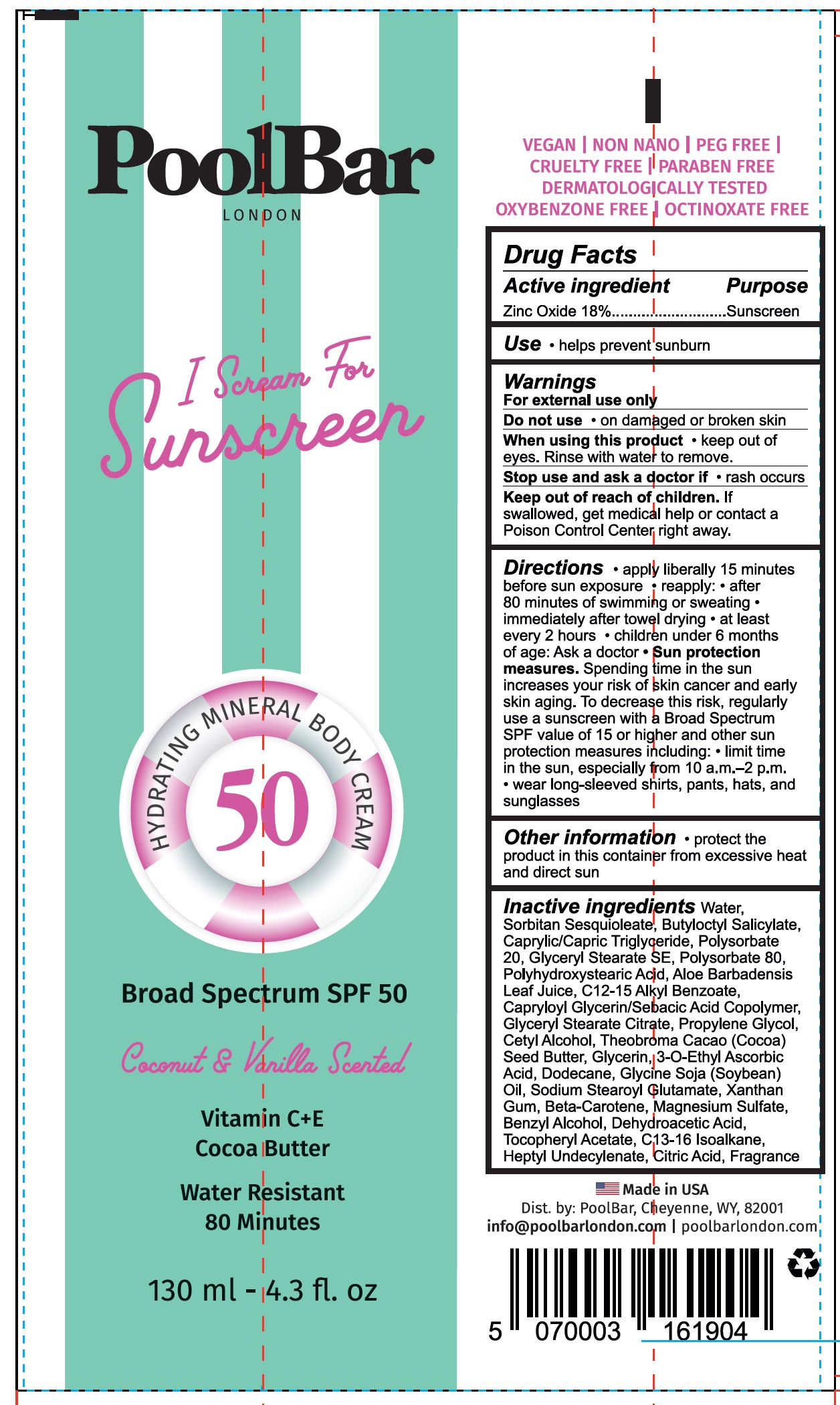 DRUG LABEL: Pool Bar London I Scream For Sunscreen Hydrating Mineral Body Cream SPF 50 Coconut and Vanilla Scented
NDC: 84953-564 | Form: CREAM
Manufacturer: POOLBAR
Category: otc | Type: HUMAN OTC DRUG LABEL
Date: 20241119

ACTIVE INGREDIENTS: ZINC OXIDE 180 mg/1 mL
INACTIVE INGREDIENTS: WATER; SORBITAN SESQUIOLEATE; BUTYLOCTYL SALICYLATE; CAPRYLIC/CAPRIC TRIGLYCERIDE; POLYSORBATE 20; GLYCERYL STEARATE SE; POLYSORBATE 80; ALOE VERA LEAF; C12-15 ALKYL BENZOATE; GLYCERYL STEARATE CITRATE; PROPYLENE GLYCOL; CETYL ALCOHOL; COCOA BUTTER; GLYCERIN; 3-O-ETHYL ASCORBIC ACID; DODECANE; SOYBEAN OIL; SODIUM STEAROYL GLUTAMATE; XANTHAN GUM; BETA-CAROTENE; MAGNESIUM SULFATE; BENZYL ALCOHOL; DEHYDROACETIC ACID; .ALPHA.-TOCOPHEROL ACETATE; C13-16 ISOPARAFFIN; HEPTYL UNDECYLENATE; CITRIC ACID MONOHYDRATE

Pool Bar London I Scream For Sunscreen Hydrating Mineral Body Cream SPF 50, Coconut & Vanilla Scented

Active ingredient

Zinc Oxide 18%

Purpose

Sunscreen

Use

- helps prevent sunburn

Warnings

For external use only

Do not use

- on damaged or broken skin

When using this product

- keep out of eyes. Rinse with water to remove.

Stop use and ask a doctor if

- rash occurs

Keep out of reach of children.

If swallowed, get medical help or contact a Poison Control Center right away.

Directions

- apply liberally 15 minutes before sun exposure
- reapply:
- after 80 minutes of swimming or sweating
- immediately after towel drying
- at least every 2 hours
- children under 6 months of age: Ask a doctor
- Sun protection measures.Spending time in the sun increases your risk of skin cancer and early skin aging. To decrease the risk, regularly use a sunscreen with a Broad Spectrum SPF of 15 or higher and other sun protection measures including:limit time in the sun, especially from 10 a.m. - 2 p.m.
- wear long-sleeved shirts, pants, hats, and sunglasses

Other information

- protect the product in this container from excessive heat and direct sun

Inactive ingredients

Water, Sorbitan Sesquioleate, Butyloctyl Salicylate, Caprylic/Capric Triglyceride, Polysorbate 20, Glyceryl Stearate SE, Polysorbate 80, Polyhydroxystearic Acid, Aloe Barbadensis Leaf Juice, C12-15 Alkyl Benzoate, Capryloyl Glycerin/Sebacic Acid Copolymer, Glyceryl Stearate Citrate, Propylene Glycol, Cetyl Alcohol, Theobroma Cacao (Cocoa) Seed Butter, Glycerin, 3-O-Ethyl Ascorbic Acid, Dodecane, Glycine Soja (Soybean) Oil, Sodium Stearoyl Glutamate, Xanthan Gum, Beta-Carotene, Magnesium Sulfate, Benzyl Alcohol, Dehydroacetic Acid, Tococpheryl Acetate, C13-16 Isoalkane, Heptyl Undecylenate, Citric Acid, Fragrance